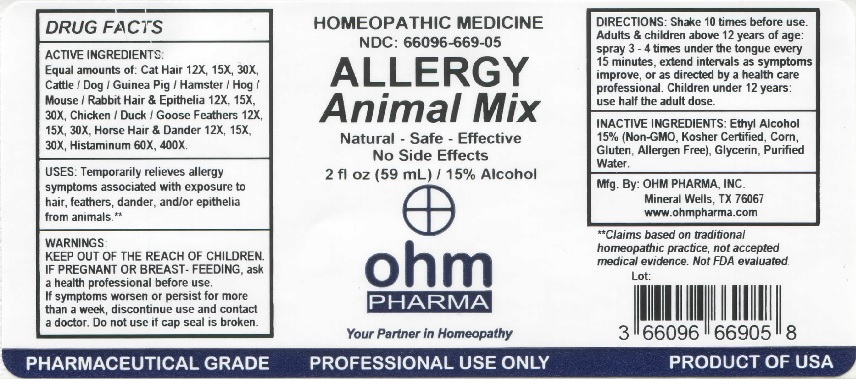 DRUG LABEL: OHM Allergy Animal Mix
NDC: 66096-669 | Form: SPRAY
Manufacturer: OHM PHARMA INC.
Category: homeopathic | Type: HUMAN OTC DRUG LABEL
Date: 20211229

ACTIVE INGREDIENTS: FELIS CATUS HAIR 12 [hp_X]/59 mL; BOS TAURUS HAIR 12 [hp_X]/59 mL; CANIS LUPUS FAMILIARIS HAIR 12 [hp_X]/59 mL; CAVIA PORCELLUS HAIR 12 [hp_X]/59 mL; MESOCRICETUS AURATUS SKIN 12 [hp_X]/59 mL; SUS SCROFA HAIR 12 [hp_X]/59 mL; MUS MUSCULUS HAIR 12 [hp_X]/59 mL; ORYCTOLAGUS CUNICULUS HAIR 12 [hp_X]/59 mL; ORYCTOLAGUS CUNICULUS SKIN 12 [hp_X]/59 mL; GALLUS GALLUS FEATHER 12 [hp_X]/59 mL; ANAS PLATYRHYNCHOS FEATHER 12 [hp_X]/59 mL; ANSER ANSER FEATHER 12 1/59 mL; EQUUS CABALLUS HAIR 12 [hp_X]/59 mL; EQUUS CABALLUS DANDER 12 [hp_X]/59 mL; HISTAMINE DIHYDROCHLORIDE 60 [hp_X]/59 mL
INACTIVE INGREDIENTS: ALCOHOL; GLYCERIN; WATER

OHM Allergy Animal Mix

ACTIVE INGREDIENT

ACTIVE INGREDIENTS: Equal amounts of: Cat Hair 12X, 15X, 30X, Cattle / Dog / Guinea Pig / Hamster / Hog / Mouse / Rabbit Hair & Epithelia 12X, 15X, 30X, Chicken / Duck / Goose Feathers 12X, 15X, 30X, Horse Hair & Dander 12X, 15X, 30X, Histaminum 60X, 400X.

INDICATIONS AND USAGE

USES: Temporarily relieves allergy symptoms associated with exposure to hair, feathers, dander, and/or epithelia from animals.**

**Claims based on traditional homeopathic practice, not accepted medical evidence. Not FDA evaluated.

WARNINGS

WARNINGS: IF PREGNANT OR BREAST-FEEDING, ask a health professional before use. If symptoms worsen or persist for more than a week, discontinue use and contact a doctor.

- KEEP OUT OF REACH OF CHILDREN.

DOSAGE AND ADMINISTRATION

DIRECTIONS: Shake 10 times before use. Adults & children above 12 years of age: spray 3-4 times under the tongue every 15 minutes, extend intervals as symptoms improve or as directed by a health care professional. Children under 12 years: use half the adult dose.

Do not use if cap seal is broken.

INACTIVE INGREDIENT

INACTIVE INGREDIENTS: Ethyl Alcohol 15% (Non-GMO, Kosher Certified, Corn, Gluten, Allergen Free), Glycerin, Purified Water.

QUESTIONS

Mfg. By: OHM PHARMA, INC. Mineral Wells, TX 76067

www.ohmpharma.com

PACKAGE LABEL

HOMEOPATHIC MEDICINE

NDC: 66096-669-05

ALLERGY

Animal Mix

Natural - Safe - Effective

No Side Effects

2 fl oz (59 mL) / 15% Alcohol

PURPOSE

Temporarily relieves allergy

symptoms associated with exposure to

hair, feathers, dander, and / or epithelia

from animals.**